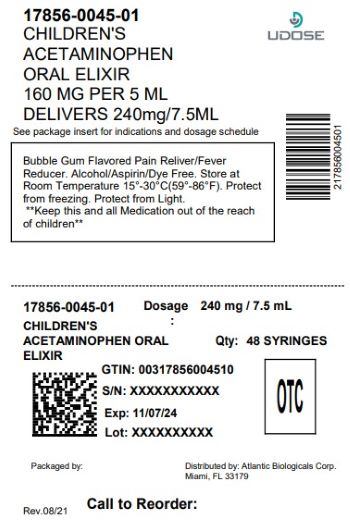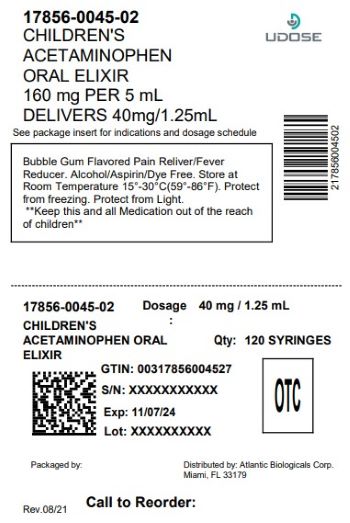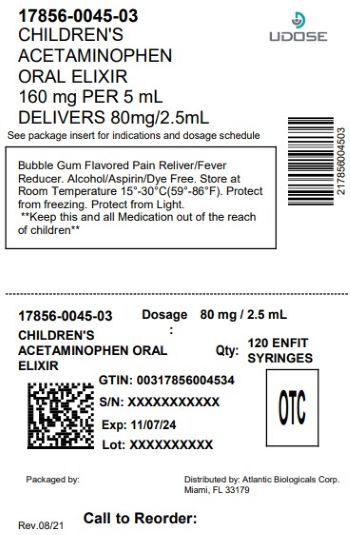 DRUG LABEL: MAX relief junior
NDC: 17856-0045 | Form: LIQUID
Manufacturer: ATLANTIC BIOLOGICALS CORP.
Category: otc | Type: HUMAN OTC DRUG LABEL
Date: 20251210

ACTIVE INGREDIENTS: ACETAMINOPHEN 160 mg/5 mL
INACTIVE INGREDIENTS: ANHYDROUS CITRIC ACID; GLYCERIN; POLYETHYLENE GLYCOL 400; PROPYLENE GLYCOL; WATER; SACCHARIN SODIUM; SODIUM BENZOATE; SODIUM CITRATE; SORBITOL; SUCRALOSE

MAX relief junior
Dye-free Children's Pain Reliever and fever reducer
Acetaminophen 160 mg per 5 mL
Alcohol Free, Aspirin Free
For Ages 2 to 11 years

Active ingredient (in each 5 mL)

Acetaminophen 160 mg

Purpose

Pain Reliever/Fever Reducer

Uses

- temporarily
- reduces fever
- relieves minor aches and pains due to:
- the common cold
- flu
- headache
- sore throat
- toothache

Warnings

Liver Warning: This product contains acetaminophen. Severe liver damage may occur if your child takes:

- more than 5 doses in 24 hours, which is the maximum daily amount
- with other drugs containing acetaminophen

Allergy alert: Acetaminophen may cause severe skin reactions.

Soar throat warning:if sore throat is severe, persists or more than 2 days, isaccompanied or followed by fever headache, rash, nausea, or vomiting, consult a doctor promptly.

Do not use

- with any other drug containing acetaminophen (prescription or nonprescription).
- If you are not sure whether a drug contains acetaminophen, ask a doctor or pharmacist.

Ask a doctor before use if your child has liver disease.

Ask a doctor or pharmacist before use if your child is taking the blood thinning drug warfarin.

When using this product: Do not exceed recommended dose (see overdose warning)

Stop use and ask a doctor if

- pain gets worse or lasts more than 5 days
- fever gets worse or lasts more than 3 days
- new symptoms occur
- redness or swelling is present. These could be signs of a serious condition.

Keep out of reach of children.

PREGNANCY OR BREAST FEEDING

If pregnant or breast-feeding, ask a health professional before use

Overdose warning. In case of overdose, get medical help or contact a Paoison Control Center (1-800-222-1222) right away. Quick medical attention is critical even if you do not notice any signs or symptoms.

Directions

- this product does not contain direction or complete warnings for adult use
- Shake well before using
- ml = milliliter
- find right dose on chart below
- if possible, use weight to dose; otherwise use age
- use only the enclosed dosing cup designed for use with this product. Do not use any other dosing device.
- if needed, repeat dose every 4 hourswhile symptoms last
- do not give more than 5 times in 24 hours
- do not give more than 5 days unless directed by doctor.

Weight (lbs.) | Age (yrs.) | Dose (tsp or mL)
under 24 | under 2 | ask a doctor
24 to 35 | 2 to 3 | 1 tsp or 5 mL
36 to 47 | 4 to 5 | 1 1/2 tsp or 7.5 mL
48 to 59 | 6 to 8 | 2 tsp or 10 mL
60 to 71 | 9 to 10 | 2 1/2 tsp or 12.5 mL
72 to 95 | 11 | 3 tsp or 15 mL

Other Information store at room temperature 15o-30oC (59o-86oF). Protect from Freezing. Protect from light.

INACTIVE INGREDIENT

Inactive ingredients: amydrous citric acid, bubble gum flavor, glycerin, polyethylene glycol400, punfied water, saccharin sodium, sodium benzoate, sodium citrate, sorbttol solution, sucralose.

QUESTIONS

DISTRIBUTED BY:

ATLANTIC BIOLOGICALS CORP.

MIAMI, FL 33179

This product is not manufactured by or distributed by McNeil Consumer Healthcare, owner of the registered trademark Tylenol Eixir.